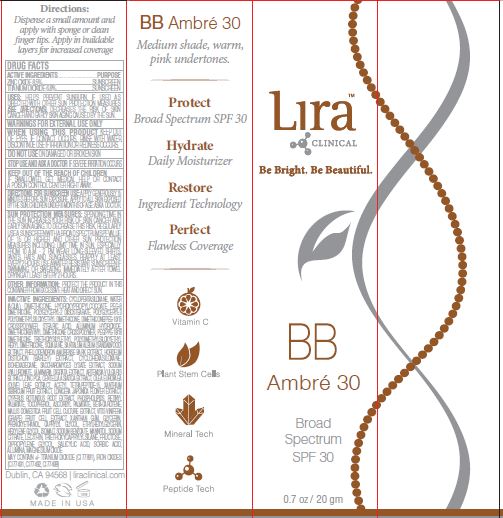 DRUG LABEL: BB Ambre 30 BS SPF30
NDC: 62742-4252 | Form: CREAM
Manufacturer: Allure Labs
Category: otc | Type: HUMAN OTC DRUG LABEL
Date: 20240314

ACTIVE INGREDIENTS: TITANIUM DIOXIDE 6.8 g/100 g; ZINC OXIDE 8.5 g/100 g
INACTIVE INGREDIENTS: LONICERA JAPONICA FLOWER; TRIETHOXYSILYLETHYL POLYDIMETHYLSILOXYETHYL HEXYL DIMETHICONE; SANDALWOOD; WATER; ETHYLHEXYLGLYCERIN; LECITHIN, SOYBEAN; DIPROPYLENE GLYCOL; ALUMINUM OXIDE; PHELLODENDRON AMURENSE BARK; BARLEY; CYCLOMETHICONE 6; SACCHAROMYCES LYSATE; ARTEMISIA VULGARIS ROOT; CYPERUS ROTUNDUS ROOT; TOCOPHEROL; SODIUM CITRATE; MAGNESIUM OXIDE; STEARIC ACID; DIMETHICONE/VINYL DIMETHICONE CROSSPOLYMER (SOFT PARTICLE); GLYCERIN; FERRIC OXIDE RED; CYCLOMETHICONE 5; DIMETHICONE; OLEA EUROPAEA LEAF; OMEGA-3 FATTY ACIDS; ASCORBYL PALMITATE; PHENOXYETHANOL; CAPRYLYL GLYCOL; HEXYLENE GLYCOL; SODIUM BENZOATE; MANNITOL; FERRIC OXIDE YELLOW; FERROSOFERRIC OXIDE; DIMETHICONE/PEG-10/15 CROSSPOLYMER; ALUMINUM HYDROXIDE; PEG/PPG-18/18 DIMETHICONE; ISOHEXADECANE; LAMINARIA DIGITATA; CENTELLA ASIATICA TRITERPENOIDS; ZINC PIDOLATE; VITAMIN A PALMITATE; APPLE; HYDROXYPROPYLCOCOATE PEG-8 DIMETHICONE; POLYGLYCERYL-2 DIISOSTEARATE; HYALURONATE SODIUM; SORBIC ACID; WINE GRAPE; XANTHAN GUM; ISOMALT; TRIETHOXYCAPRYLYLSILANE; FRUCTOSE; SQUALANE; POLYGLYCERYL-3 POLYDIMETHYLSILOXYETHYL DIMETHICONE (4000 MPA.S); ACETYL TETRAPEPTIDE-15; XANTHIUM SIBIRICUM FRUIT; BETA CAROTENE; SALICYLIC ACID

Drug Facts

ACTIVE INGREDIENTS

ZINC OXIDE 8.5%

TITANIUM DIOXIDE 6.8%

PURPOSE:

SUNSCREEN

INDICATIONS AND USAGE

USES: HELPS PREVENT SUNBURN. IF USED AS DIRECTED WITH OTHER SUN PROTECTION MEASURES (SEE DIRECTIONS), DECREASES THE RISK OF SKIN CANCER AND EARLY SKIN AGING CAUSED BY THE SUN.

WARNINGS FOR EXTERNAL USE ONLY

DO NOT USEON DAMAGED OR BROKEN SKIN

WHEN USING THIS PRODUCT KEEP OUT OF EYES. IF CONTACT OCCURS, RINSE WITH WATER. DISCONTINUE USE IF IRRITATION OR REDNESS OCCURS.

STOP USE AND ASK A DOCTOR IF SEVERE IRRITATION OCCURS

KEEP OUT OF REACH OF CHILDREN

KEEP OUT OF THE REACH OF CHILDREN IF SWALLOWED, GET MEDICAL HELP OR CONTACT A POISON CONTROL CENTER RIGHT AWAY.

DOSAGE AND ADMINISTRATION

DIRECTIONS FOR SUNSCREEN USE: APPLY GENEROUSLY 15 MINUTES BEFORE SUN EXPOSURE. APPLY TO ALL SKIN EXPOSED BY THE SUN. CHILDREN UNDER 6 MONTHS OF AGE: ASK A DOCTOR. SUN PROTECTION MEASURES: SPENDING TIME IN THE SUN INCREASES YOUR RISK OF SKIN CANCER AND EARLY SKIN AGING. TO DECREASE THIS RISK, REGULARLY USE A SUNSCREEN WITH A BROAD SPECTRUM SPF VALUE OF 15 OR HIGHER AND OTHER SUN PROTECTION MEASURES INCLUDING: LIMIT TIME IN SUN, ESPECIALLY FROM 10 A.M. - 2 P.M. WEAR LONG-SLEEVED SHIRTS, PANTS, HATS AND SUNGLASSES. REAPPLY AT LEAST EVERY 2 HOURS. USE A WATER RESISTANT SUNSCREEN IF SWIMMING OR SWEATING IMMEDIATELY AFTER TOWEL DRYING AT LEAST EVERY 2 HOURS.

OTHER INFORMATION: PROTECT THE PRODUCT IN THIS CONTAINER FROM EXCESSIVE HEAT AND DIRECT SUN.

INACTIVE INGREDIENT

INACTIVE INGREDIENTS: CYCLOPENTASILOXANE, WATER (AQUA), DIMETHICONE, HYDROXYPROPYLCOCOATE PEG-8 DIMETHICONE, POLYGLYCERYL-2 DIISOSTEARATE, POLYGLYCERYL-3 POLYDIMETHYLSILOXYETHYL DIMETHICONE, DIMETHICONE/PEG-10/15 CROSSPOLYMER, STEARIC ACID, ALUMINUM HYDROXIDE, DIMETHICONE/VINYL DIMETHICONE CROSSPOLYMER, PEG/PPG-18/18DIMETHICONE, TRIETHOXYSILYLETHYL POLYDIMETHYLSILOXYETHYL HEXYL DIMETHICONE, SQUALANE, SANTALUM ALBUM (SANDALWOOD) EXTRACT, PHELLODENDRON AMURENSE BARK EXTRACT, HORDEUM DISTICHON (BARLEY) EXTRACT, CYCLOHEXASILOXANE, ISOHEXADECANE, SACCHAROMYCES LYSATE EXTRACT, SODIUM HYALURONATE, LAMINARIA DIGITATA EXTRACT, ARTEMISIA VULGARIS EXTRACT, ZINC PCA, CENTELLA ASIATICA EXTRACT, OLEA EUROPAEA (OLIVE) LEAF EXTRACT, ACETYL TETRAPEPTIDE-15, XANTHIUM SIBIRICUM FRUIT EXTRACT, LONICERA JAPONICA FLOWER EXTRACT, CYPERUS ROTUNDUS ROOT EXTRACT, PHOSPHOLIPIDS, RETINYL PALMITATE, TOCOPHEROL, ASCORBYL PALMITATE, BETA-CAROTENE, MALUS DOMESTICA FRUIT CELL CULTURE EXTRACT, VITIS VINIFERA (GRAPE) FRUIT CELL EXTRACT, XANTHAN GUM, GLYCERIN, PHENOXYETHANOL, CAPRYLYL GLYCOL, ETHYLHEXYLGLYCERIN, HEXYLENE GLYCOL, ISOMALT, SODIUM BENZOATE, MANNITOL, SODIUM CITRATE, LECITHIN, TRIETHOXYCAPRYLYLSILANE, FRUCTOSE, DIPROPYLENE GLYCOL, SALICYLIC ACID, SORBIC ACID, ALUMINA, MAGNESIUM OXIDE MAY CONTAIN +/- TITANIUM DIOXIDE (CI 77891), IRON OXIDES (CI 77491, CI 77492, CI 77499)